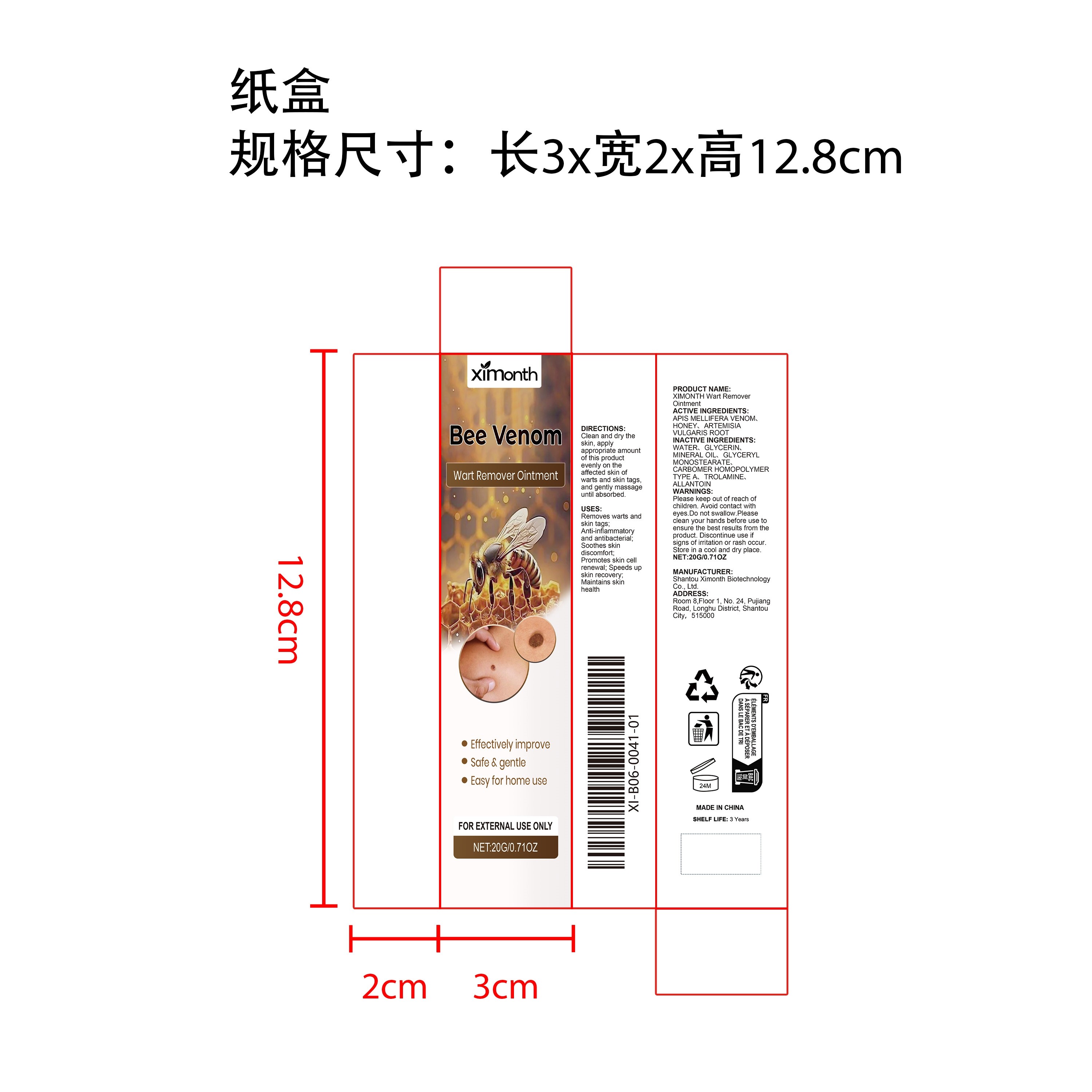 DRUG LABEL: XIMONTH Wart Remover
NDC: 84989-004 | Form: OINTMENT
Manufacturer: Shantou Ximonth Biotechnology Co., Ltd.
Category: otc | Type: HUMAN OTC DRUG LABEL
Date: 20251126

ACTIVE INGREDIENTS: ARTEMISIA VULGARIS ROOT 0.004 mg/20 mg; APIS MELLIFERA VENOM 0.004 mg/20 mg; HONEY 0.004 mg/20 mg
INACTIVE INGREDIENTS: MINERAL OIL 1 mg/20 mg; CARBOMER HOMOPOLYMER TYPE A 0.04 mg/20 mg; ALLANTOIN 0.004 mg/20 mg; GLYCERIN 1.6 mg/20 mg; GLYCERYL MONOSTEARATE 0.4 mg/20 mg; TROLAMINE 0.04 mg/20 mg; WATER 16.904 mg/20 mg

ACTIVE INGREDIENT

APIS MELLIFERA VENOM、HONEY、ARTEMISIA VULGARIS ROOT

PURPOSE

Removes warts and skin tags; Anti-inflammatory and antibacterial; Soothes skin discomfort; Promotes skin cell renewal; Speeds up skin recovery; Maintains skin health

STOP USE

Discontinue use if signs of irritation or rash occur.

DO NOT USE

Discontinue use if signs of irritation or rash occur.

WHEN USING

Clean and dry the skin, apply appropriate amount of this product evenly on the affected skin of warts and skin tags, and gently massage until absorbed.

KEEP OUT OF REACH OF CHILDREN

Please keep out of reach of children. Do not swallow.

INACTIVE INGREDIENT

WATER、GLYCERIN、MINERAL OIL、GLYCERYL MONOSTEARATE、CARBOMER HOMOPOLYMER TYPE A、TROLAMINE、ALLANTOIN

WARNINGS

Please keep out of reach of children. Do not swallow.Please clean your hands before use to ensure the best results from the product. Discontinue use if signs of irritation or rash occur. Store in a cool and dry place.

STORAGE AND HANDLING

Store in a cool and dry place.